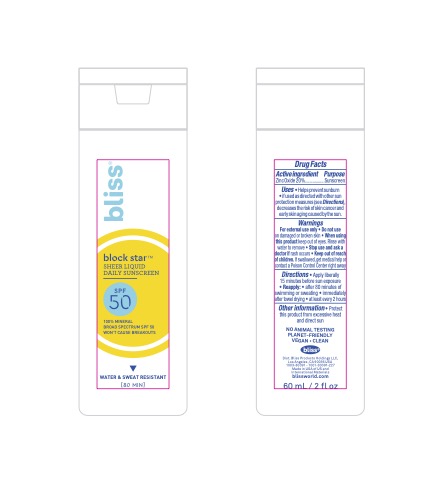 DRUG LABEL: Bliss Block Star Sheer Liquid Daily Sunscreen SPF 50
NDC: 67038-203 | Form: LOTION
Manufacturer: Bliss Products Holdings LLC
Category: otc | Type: HUMAN OTC DRUG LABEL
Date: 20241021

ACTIVE INGREDIENTS: ZINC OXIDE 20 g/100 mL
INACTIVE INGREDIENTS: CAPRYLIC/CAPRIC ACID; WATER; POLYSORBATE 60; POLYSORBATE 80; ISOHEXADECANE; GLUCONOLACTONE; VINYLPYRROLIDONE/HEXADECENE COPOLYMER; SUNFLOWER OIL; XANTHAN GUM; ETHYL FERULATE; HYDROXYETHYL ACRYLATE/SODIUM ACRYLOYLDIMETHYL TAURATE COPOLYMER (45000 MPA.S AT 1%); PHENOXYETHANOL; OLIVE OIL POLYGLYCERYL-6 ESTERS; SODIUM STEAROYL LACTYLATE; TRIETHOXYCAPRYLYLSILANE; TETRASODIUM GLUTAMATE DIACETATE; SODIUM BENZOATE; GLYCERIN; PEG-20 SORBITAN ISOSTEARATE; BISABOLOL OXIDE A; CETOSTEARYL ALCOHOL

Bliss Block Star Sheer Liquid Daily Sunscreen SPF 50

ACTIVE INGREDIENT

Zinc Oxide 20%

PURPOSE

Sunscreen

INDICATIONS AND USAGE

• Helps prevent sunburn
• if used as directed with other sun protection measures (see Directions), decreases the risk of skin cancer and early skin aging caused by the sun

WARNINGS

For external use only
• Do not use on damaged or broken skin • When using this product keep out of eyes. Rinse with water to remove
• Stop use and ask a doctor if rash occurs

• Keep out of reach of children. If swallowed, get medical help or contact a Poison Control Center right away

DOSAGE AND ADMINISTRATION

• Apply liberally 15 minutes before sun exposure • Reapply: • after 80 minutes of swimming or sweating • immediately after towel drying • at least every 2 hours • Sun Protection Measures. Spending time in the sun increases your risk of skin cancer and early skin aging. To decrease this risk, regularly use a sunscreen with a Broad Spectrum SPF value of 15 or higher and other sun protection measures including:
• limit time in the sun, especially from 10 a.m. – 2 p.m. • wear long-sleeved shirts, pants, hats and sunglasses

STORAGE AND HANDLING

• Protect this product from excessive heat and direct sun

INACTIVE INGREDIENT

Water, Caprylic/Capric Triglyceride, Glycerin, VP/Hexadecene Copolymer, Dimethicone, Sorbitan Isostearate, Helianthus Annuus (Sunflower) Seed Oil, Bisabolol, Xanthan Gum, Cetearyl Alcohol, Ethyl Ferulate, Olive Oil Polyglyceryl-6 Esters, Hydroxyethyl Acrylate/Sodium Acryloyldimethyl Taurate Copolymer, Glyceryl Stearate, Polysorbate 60, Polysorbate 80, Sodium Stearoyl Lactylate, Triethoxycaprylylsilane, Isohexadecane, Gluconolactone, Tetrasodium Glutamate Diacetate, Phenoxyethanol, Sodium Benzoate